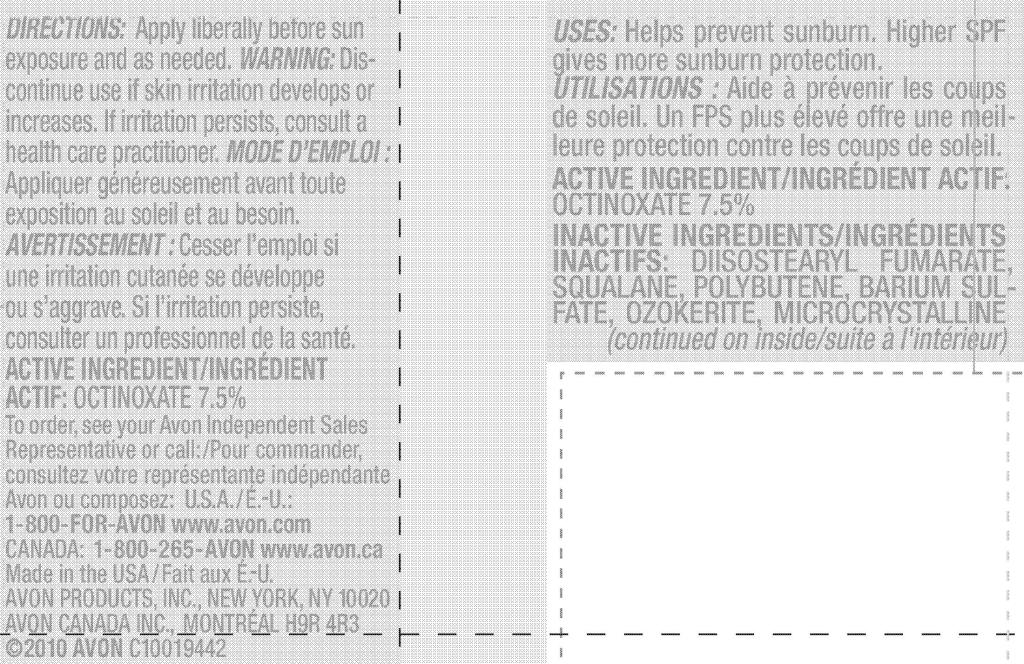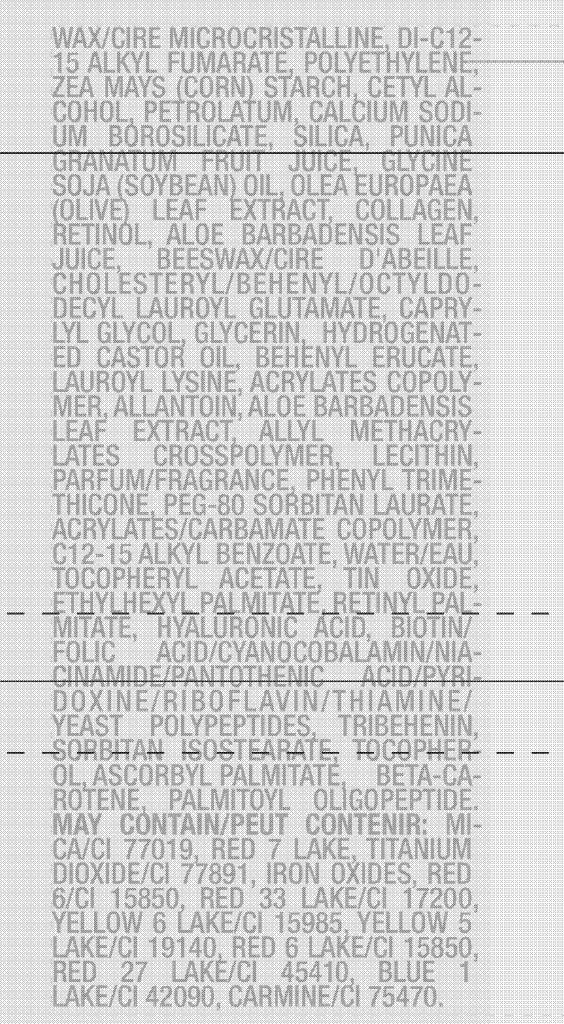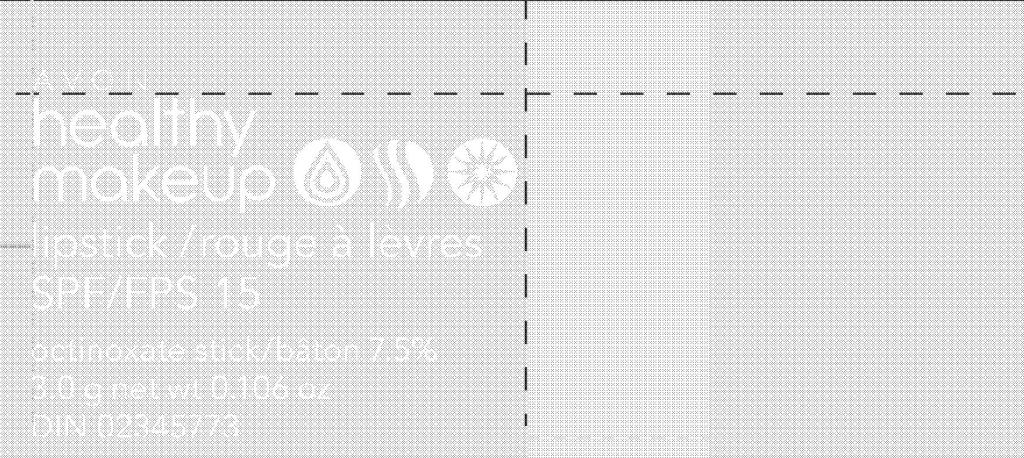 DRUG LABEL: Healthy Makeup
NDC: 10096-0216 | Form: LIPSTICK
Manufacturer: Avon Products, Inc.
Category: otc | Type: HUMAN OTC DRUG LABEL
Date: 20100610

ACTIVE INGREDIENTS: OCTINOXATE 225 mg/3 g
INACTIVE INGREDIENTS: SQUALANE; BARIUM SULFATE; CETYL ALCOHOL; PETROLATUM; RETINOL; CAPRYLYL GLYCOL; GLYCERIN; HYDROGENATED CASTOR OIL; ALLANTOIN; PHENYL TRIMETHICONE; C12-15 ALKYL BENZOATE; WATER; ETHYLHEXYL PALMITATE; HYALURONIC ACID; ASCORBYL PALMITATE ; BETA CAROTENE; MICA; TITANIUM DIOXIDE

DOSAGE AND ADMINISTRATION

DIRECTIONS: Apply liberally before sun
exposure and as needed.

WARNINGS

WARNING: Discontinue use if skin irritation
develops or increases. If irritation
persists, consult a health care
practitioner.

ACTIVE INGREDIENT/INGREDIENT ACTIF:
OCTINOXATE 7.5%

INDICATIONS AND USAGE

USES: Helps prevent sunburn. Higher SPF
gives more sunburn protection.

INACTIVE INGREDIENTS/INGREDIENTS INACTIFS:

DIISOSTEARYL FUMARATE
SQUALANE
POLYBUTENE
BARIUM SULFATE
OZOKERITE
MICROCRYSTALLINE WAX/CIRE MICROCRISTALLINE
DI-C12-15 ALKYL FUMARATE
POLYETHYLENE
ZEA MAYS (CORN) STARCH
CETYL ALCOHOL
PETROLATUM
CALCIUM SODIUM BOROSILICATE
SILICA
PUNICA GRANATUM FRUIT JUICE
GLYCINE SOJA (SOYBEAN) OIL
OLEA EUROPAEA (OLIVE) LEAF EXTRACT
COLLAGEN
RETINOL
ALOE BARBADENSIS LEAF JUICE
BEESWAX/CIRE D'ABEILLE
CHOLESTERYL/BEHENYL/OCTYLDODECYL LAUROYL GLUTAMATE
CAPRYLYL GLYCOL
GLYCERIN
HYDROGENATED CASTOR OIL
BEHENYL ERUCATE
LAUROYL LYSINE
ACRYLATES COPOLYMER
ALLANTOIN
ALOE BARBADENSIS LEAF EXTRACT
ALLYL METHACRYLATES CROSSPOLYMER
LECITHIN
PARFUM/FRAGRANCE
PHENYL TRIMETHICONE
PEG-80 SORBITAN LAURATE
ACRYLATES/CARBAMATE COPOLYMER
C12-15 ALKYL BENZOATE
WATER/EAU
TOCOPHERYL ACETATE
TIN OXIDE
ETHYLHEXYL PALMITATE
RETINYL PALMITATE
HYALURONIC ACID
Biotin/Folic Acid/Cyanocobalamin/Niacinamide/Pantothenic Acid/Pyridoxine/Riboflavin/Thiamine/Yeast Polypeptides
TRIBEHENIN
SORBITAN ISOSTEARATE
TOCOPHEROL
ASCORBYL PALMITATE
BETA-CAROTENE
PALMITOYL OLIGOPEPTIDE
MAY CONTAIN:
MICA/CI 77019
RED 7 LAKE
TITANIUM DIOXIDE/CI 77891
IRON OXIDES
RED 6/CI 15850
RED 33 LAKE/CI 17200
YELLOW 6 LAKE/CI 15985
YELLOW 5 LAKE/CI 19140
RED 6 LAKE/CI 15850
RED 27 LAKE/CI 45410
BLUE 1 LAKE/CI 42090
CARMINE/CI 75470